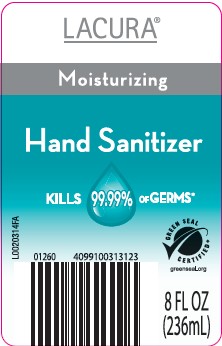 DRUG LABEL: Alcohol
NDC: 64024-849 | Form: LIQUID
Manufacturer: Aldi, Inc
Category: otc | Type: HUMAN OTC DRUG LABEL
Date: 20260129

ACTIVE INGREDIENTS: ALCOHOL 62 mg/100 mL
INACTIVE INGREDIENTS: WATER; CARBOMER HOMOPOLYMER, UNSPECIFIED TYPE; CARBOMER INTERPOLYMER TYPE A (ALLYL SUCROSE CROSSLINKED); GLYCERIN; ISOPROPYL MYRISTATE; TOCOPHEROL

Lacura 849.001/849AE
Moisturizing Hand Sanitizer

Active ingredient

Ethyl Alcohol 62%

Purpose

Antiseptic

Uses

- to decrease bacteria on the skin that could cause disease
- recommended for repeated use

Warnings

For exterenal use only: hands

Flammable, keep away from fire or flame.

When using this product

- keep out of eyes. In case of contact with eyes, flush thoroughly with water.
- avoid contact with broken skin
- do not inhale or ingest

Stop use and ask a doctor if

- irritation and redness develop
- condition persists for more than 72 hours

Keep out of reach of children.

If swallowed, get medical help or contact a Poison Control Center right away.

Directions

- wet hands thoroughly with product and allow to dry without wiping
- for children under 6, use only under adult supervision
- not recommended for infants

Other information

- do not store above 105⁰F
- may discolor some fabrics
- harmful to wood finishes and plastics

Inactive ingredients

water, carbomer and/or acrylates/C10-30 alkyl acrylate crosspolymer, fragrance, glycerin, isopropyl myristate, tocopheryl acetate

*Effective at eliminating 99.99% of many common harmful germs and bacteria in as little as 15 seconds.

Dist. & Sold Exclusively By: ALDI

Batavia, IL 60510

ALDI TWICE AS NICE GUARANTEE

items replaced

money refunded

Empty & Discard Pump

PLASTIC BOTTLE

how2recycle.info

principal display panel

LACURA®

Moisturizing

Hand Sanitizer

KILLS 99.99% OF GERMS*

GREEN SEAL CERTIFIED®

greenseal.org

8 FL. OZ (236 mL)